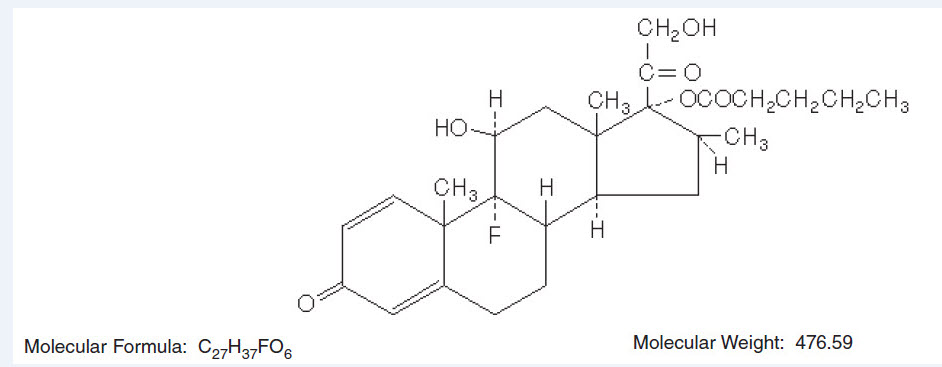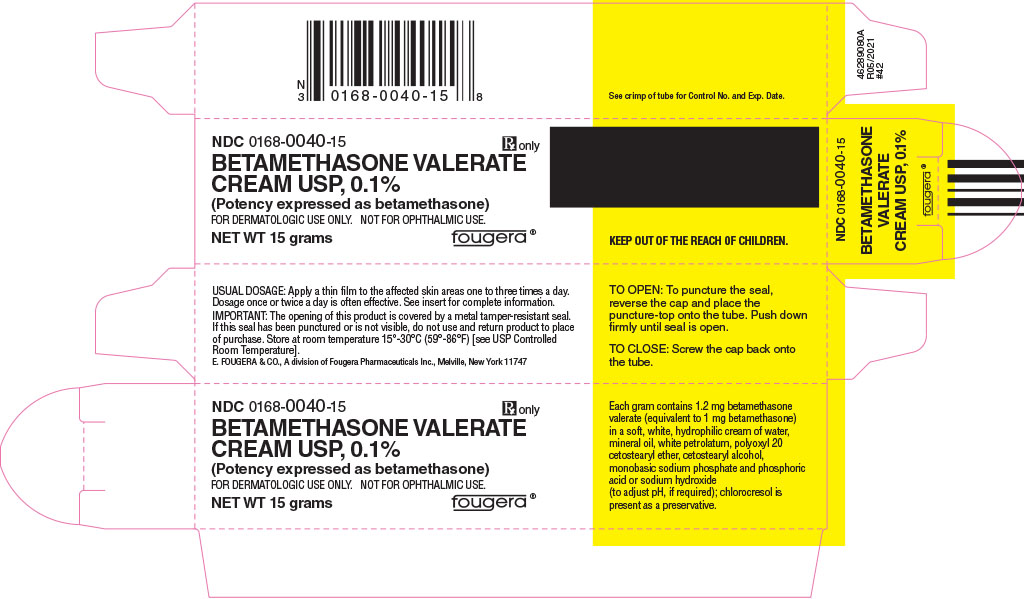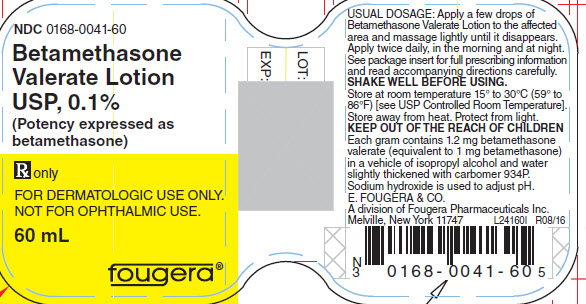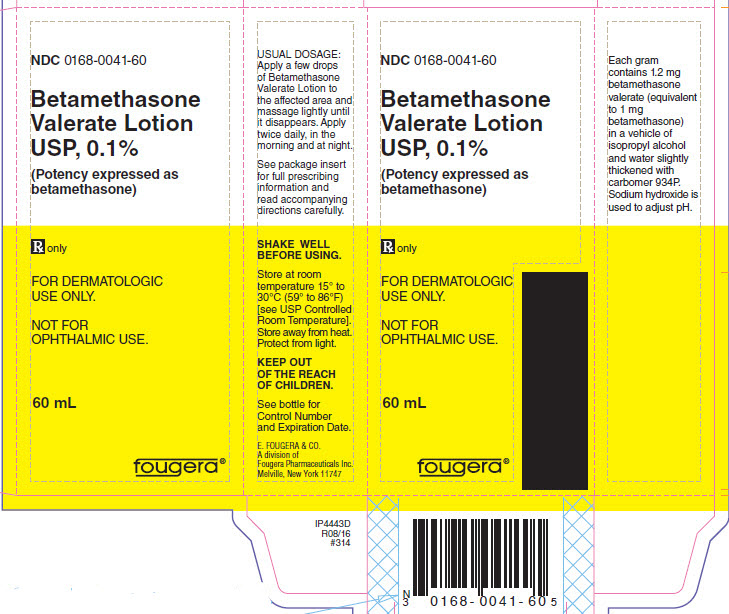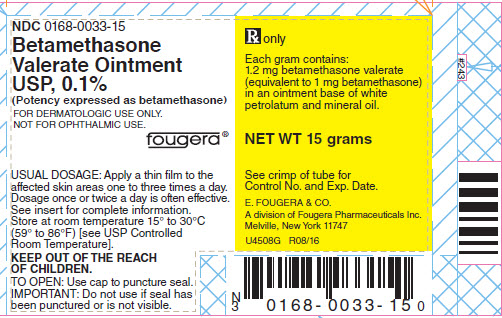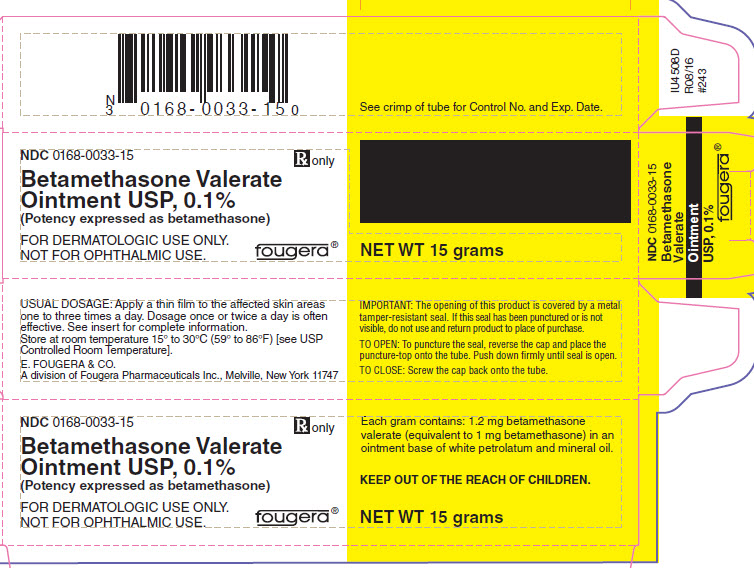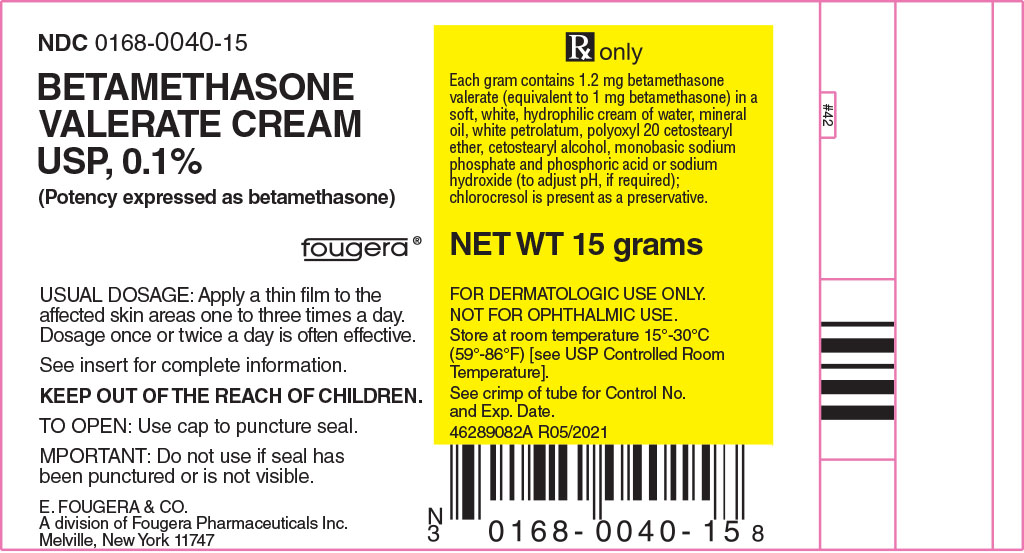 DRUG LABEL: Betamethasone Valerate
NDC: 0168-0040 | Form: CREAM
Manufacturer: E. Fougera & Co. a division of Fougera Pharmaceuticals, LLC
Category: prescription | Type: HUMAN PRESCRIPTION DRUG LABEL
Date: 20260128

ACTIVE INGREDIENTS: BETAMETHASONE VALERATE 1 mg/1 g
INACTIVE INGREDIENTS: WATER; MINERAL OIL; PETROLATUM; CETOSTEARYL ALCOHOL; POLYOXYL 20 CETOSTEARYL ETHER; SODIUM PHOSPHATE, MONOBASIC, UNSPECIFIED FORM; PHOSPHORIC ACID; SODIUM HYDROXIDE; CHLOROCRESOL

BETAMETHASONE VALERATE CREAM USP, 0.1%
BETAMETHASONE VALERATE OINTMENT USP, 0.1%
BETAMETHASONE VALERATE LOTION USP, 0.1%
(Potency expressed as betamethasone)

Rx only

FOR DERMATOLOGIC USE ONLY.
NOT FOR OPHTHALMIC USE.

DESCRIPTION:

Betamethasone Valerate Cream, Ointment and Lotion contain betamethasone valerate USP, a synthetic adrenocorticosteroid for dermatologic use. Betamethasone, an analog of prednisolone, has a high degree of glucocorticoid activity and a slight degree of mineralocorticoid activity.

Betamethasone valerate is a white to practically white odorless crystalline powder practically insoluble in water, freely soluble in acetone and chloroform, soluble in alcohol, and slightly soluble in benzene and ether. Chemically, it is 9-fluoro-11β,17,21-trihydroxy-16β-methylpregna-1, 4-diene-3,20-dione 17-valerate. The structural formula is:

Each gram of the 0.1% Cream contains 1.2 mg betamethasone valerate (equivalent to 1 mg betamethasone) in a soft, white, hydrophilic cream of purified water, mineral oil, white petrolatum, polyoxyl 20 cetostearyl ether, cetostearyl alcohol, monobasic sodium phosphate and phosphoric acid or sodium hydroxide (to adjust pH, if required); chlorocresol is present as a preservative.

Each gram of the 0.1% Ointment contains 1.2 mg betamethasone valerate (equivalent to 1 mg betamethasone) in an ointment base of white petrolatum and mineral oil.

Each gram of the 0.1% Lotion contains 1.2 mg betamethasone valerate (equivalent to 1 mg betamethasone) in a vehicle of isopropyl alcohol and water slightly thickened with carbomer 934P. Sodium hydroxide is used to adjust pH.

CLINICAL PHARMACOLOGY:

Topical corticosteroids share anti-inflammatory, antipruritic and vasoconstrictive actions.

The mechanism of anti-inflammatory activity of the topical corticosteroids is unclear. Various laboratory methods, including vasoconstrictor assays, are used to compare and predict potencies and/or clinical efficacies of the topical corticosteroids. There is some evidence to suggest that a recognizable correlation exists between vasoconstrictor potency and therapeutic efficacy in man.

PHARMACOKINETICS

Pharmacokinetics: The extent of percutaneous absorption of topical corticosteroids is determined by many factors including the vehicle, the integrity of the epidermal barrier, and the use of occlusive dressings.

Topical corticosteroids can be absorbed from normal intact skin. Inflammation and/or other disease processes in the skin increase percutaneous absorption. Occlusive dressings substantially increase the percutaneous absorption of topical corticosteroids. Thus, occlusive dressings may be a valuable therapeutic adjunct for treatment of resistant dermatoses.

Once absorbed through the skin, topical corticosteroids are handled through pharmacokinetic pathways similar to systemically administered corticosteroids. Corticosteroids are bound to plasma proteins in varying degrees. Corticosteroids are metabolized primarily in the liver and are then excreted by the kidneys. Some of the topical corticosteroids and their metabolites are also excreted into the bile.

INDICATIONS AND USAGE:

Topical corticosteroids are indicated for the relief of the inflammatory and pruritic manifestations of corticosteroid-responsive dermatoses.

CONTRAINDICATIONS:

Topical corticosteroids are contraindicated in those patients with a history of hypersensitivity to any of the components of the preparation.

PRECAUTIONS:

GENERAL PRECAUTIONS

General: Systemic absorption of topical corticosteroids has produced reversible hypothalamic-pituitary-adrenal (HPA) axis suppression, manifestations of Cushing's syndrome, hyperglycemia, and glucosuria in some patients.

Conditions which augment systemic absorption include the application of the more potent steroids, use over large surface areas, prolonged use, and the addition of occlusive dressings.

Therefore, patients receiving a large dose of a potent topical steroid applied to a large surface area should be evaluated periodically for evidence of HPA axis suppression by using the urinary free cortisol and ACTH stimulation tests. If HPA axis suppression is noted, an attempt should be made to withdraw the drug, to reduce the frequency of application, or substitute to a less potent steroid.

Recovery of HPA axis function is generally prompt and complete upon discontinuation of the drug. Infrequently, signs and symptoms of steroid withdrawal may occur, requiring supplemental systemic corticosteroids.

Pediatric patients may absorb proportionally larger amounts of topical corticosteroids and thus be more susceptible to systemic toxicity (See PRECAUTIONS—Pediatric Use).

If irritation develops, topical corticosteroids should be discontinued and appropriate therapy instituted.

In the presence of dermatological infections, the use of an appropriate antifungal or antibacterial agent should be instituted. If a favorable response does not occur promptly, the corticosteroid should be discontinued until the infection has been adequately controlled.

PATIENT COUNSELING INFORMATION

Information for Patients: Patients using topical corticosteroids should receive the following information and instructions:

1. This medication is to be used as directed by the physician. It is for external use only. Avoid contact with the eyes.
2. Patients should be advised not to use this medication for any disorder other than that for which it was prescribed.
3. The treated skin area should not be bandaged or otherwise covered or wrapped as to be occlusive unless directed by the physician.
4. Patients should report any signs of local adverse reactions especially under occlusive dressing.
5. Parents of pediatric patients should be advised not to use tight-fitting diapers or plastic pants on a child being treated in the diaper area, as these garments may constitute occlusive dressings.

LABORATORY TESTS

Laboratory tests: The following tests may be helpful in evaluating the HPA axis suppression:

Urinary free cortisol test
ACTH stimulation test

CARCINOGENESIS AND MUTAGENESIS AND IMPAIRMENT OF FERTILITY

Carcinogenesis, Mutagenesis and Impairment of Fertility: Long-term animal studies have not been performed to evaluate the carcinogenic potential or the effect on fertility of topical corticosteroids.

Studies to determine mutagenicity with prednisolone and hydrocortisone have revealed negative results.

TERATOGENIC EFFECTS

Pregnancy: Teratogenic Effects — Pregnancy Category C. Corticosteroids are generally teratogenic in laboratory animals when administered systemically at relatively low dosage levels. The more potent corticosteroids have been shown to be teratogenic after dermal application in laboratory animals. There are no adequate and well-controlled studies in pregnant women on teratogenic effects from topically applied corticosteroids. Therefore, topical corticosteroids should be used during pregnancy only if the potential benefit justifies the potential risk to the fetus. Drugs of this class should not be used extensively on pregnant patients, in large amounts, or for prolonged periods of time.

NURSING MOTHERS

Nursing Mothers: It is not known whether topical administration of corticosteroids could result in sufficient systemic absorption to produce detectable quantities in breast milk. Systemically administered corticosteroids are secreted into breast milk in quantities not likely to have a deleterious effect on the infant. Nevertheless, caution should be exercised when topical corticosteroids are administered to a nursing woman.

PEDIATRIC USE

Pediatric Use: Pediatric patients may demonstrate greater susceptibility to topical corticosteroid-induced HPA axis suppression and Cushing's syndrome than mature patients because of a larger skin surface area to body weight ratio.

Hypothalamic-pituitary-adrenal (HPA) axis suppression, Cushing's syndrome, and intracranial hypertension have been reported in children receiving topical corticosteroids. Manifestations of adrenal suppression in children include linear growth retardation, delayed weight gain, low plasma cortisol levels, and absence of response to ACTH stimulation. Manifestations of intracranial hypertension include bulging fontanelles, headaches, and bilateral papilledema.

Administration of topical corticosteroids to pediatric patients should be limited to the least amount compatible with an effective therapeutic regimen. Chronic corticosteroid therapy may interfere with the growth and development of children.

ADVERSE REACTIONS:

The following local adverse reactions are reported infrequently with topical corticosteroids, but may occur more frequently with the use of occlusive dressings. These reactions are listed in an approximate decreasing order of occurrence: burning, itching, irritation, dryness, folliculitis, hypertrichosis, acneiform eruptions, hypopigmentation, perioral dermatitis, allergic contact dermatitis, maceration of the skin, secondary infection, skin atrophy, striae and miliaria.

OVERDOSAGE:

Topically applied corticosteroids can be absorbed in sufficient amounts to produce systemic effects (See PRECAUTIONS).

DOSAGE AND ADMINISTRATION:

Apply a thin film of Betamethasone Valerate Cream or Ointment to the affected skin areas one to three times a day. Dosage once or twice a day is often effective.

Apply a few drops of Betamethasone Valerate Lotion to the affected area and massage lightly until it disappears. Apply twice daily, in the morning and at night. Dosage may be increased in stubborn cases. Following improvement, apply once daily. For the most effective and economical use, apply nozzle very close to affected area and gently squeeze bottle.

HOW SUPPLIED:

Betamethasone Valerate | Betamethasone Valerate | Betamethasone Valerate
Cream USP, 0.1% | Ointment USP, 0.1% | Lotion USP, 0.1%
is supplied as follows: | is supplied as follows: | is supplied as follows:
15 g tubes NDC 0168-0040-15 | 15 g tubes NDC 0168-0033-15 | 60 mL bottles NDC 0168-0041-60
45 g tubes NDC 0168-0040-46 | 45 g tubes NDC 0168-0033-46 | Shake well before using. Store away from heat and protect from light.

Store at room temperature 15° - 30°C (59° - 86°F) [see USP Controlled Room Temperature].

E. FOUGERA & CO.
A division of
Fougera
PHARMACEUTICALS INC.
Melville, NY 11747

46289058A
R06/2021
#57

PACKAGE LABEL – PRINCIPAL DISPLAY PANEL – 15 GRAM CONTAINER

NDC 0168-0040-15

Fougera®

BETAMETHASONE
VALERATE CREAM
USP, 0.1%
(Potency expressed as betamethasone)

Rx only

NET WT 15 grams

PACKAGE LABEL – PRINCIPAL DISPLAY PANEL – 15 GRAM CARTON

NDC 0168-0040-15

Rx only

Fougera®

BETAMETHASONE VALERATE
CREAM USP, 0.1%
(Potency expressed as betamethasone)

FOR DERMATOLOGIC
USE ONLY.
NOT FOR OPHTHALMIC USE.

WARNING: Keep out of
reach of children.

NET WT 15 grams

PACKAGE LABEL – PRINCIPAL DISPLAY PANEL – 60 ML CONTAINER

NDC 0168-0041-60

Fougera®

BETAMETHASONE
VALERATE
LOTION USP, 0.1%
(Potency expressed as betamethasone)

60 mL

FOR DERMATOLOGIC USE ONLY.
NOT FOR OPHTHALMIC USE.

Rx only

PACKAGE LABEL – PRINCIPAL DISPLAY PANEL – 60 ML CARTON

NDC 0168-0041-60

Fougera®

BETAMETHASONE
VALERATE
LOTION USP, 0.1%
(Potency expressed as
betamethasone)

60 mL

FOR DERMATOLOGIC USE ONLY.
NOT FOR OPHTHALMIC USE.

Rx only

PACKAGE LABEL – PRINCIPAL DISPLAY PANEL – 15 GRAM CONTAINER

NDC 0168-0033-15

Fougera®

BETAMETHASONE
VALERATE OINTMENT
USP, 0.1%
(Potency expressed as betamethasone)

Rx only

NET WT 15 grams

PACKAGE LABEL – PRINCIPAL DISPLAY PANEL – 15 GRAM CARTON

NDC 0168-0033-15

Rx only

Fougera®

BETAMETHASONE VALERATE
OINTMENT USP, 0.1%
(Potency expressed as betamethasone)

FOR DERMATOLOGIC
USE ONLY.
NOT FOR OPHTHALMIC USE.

WARNING: Keep out of
reach of children.

NET WT 15 grams